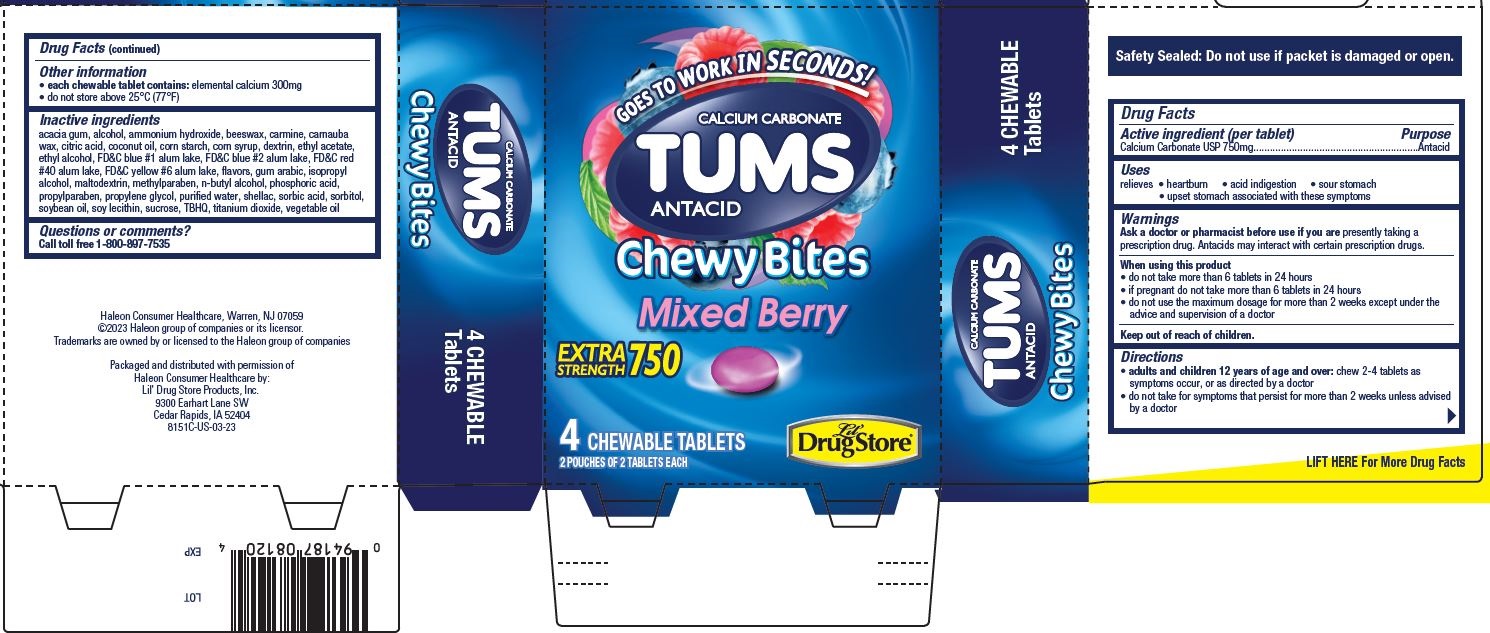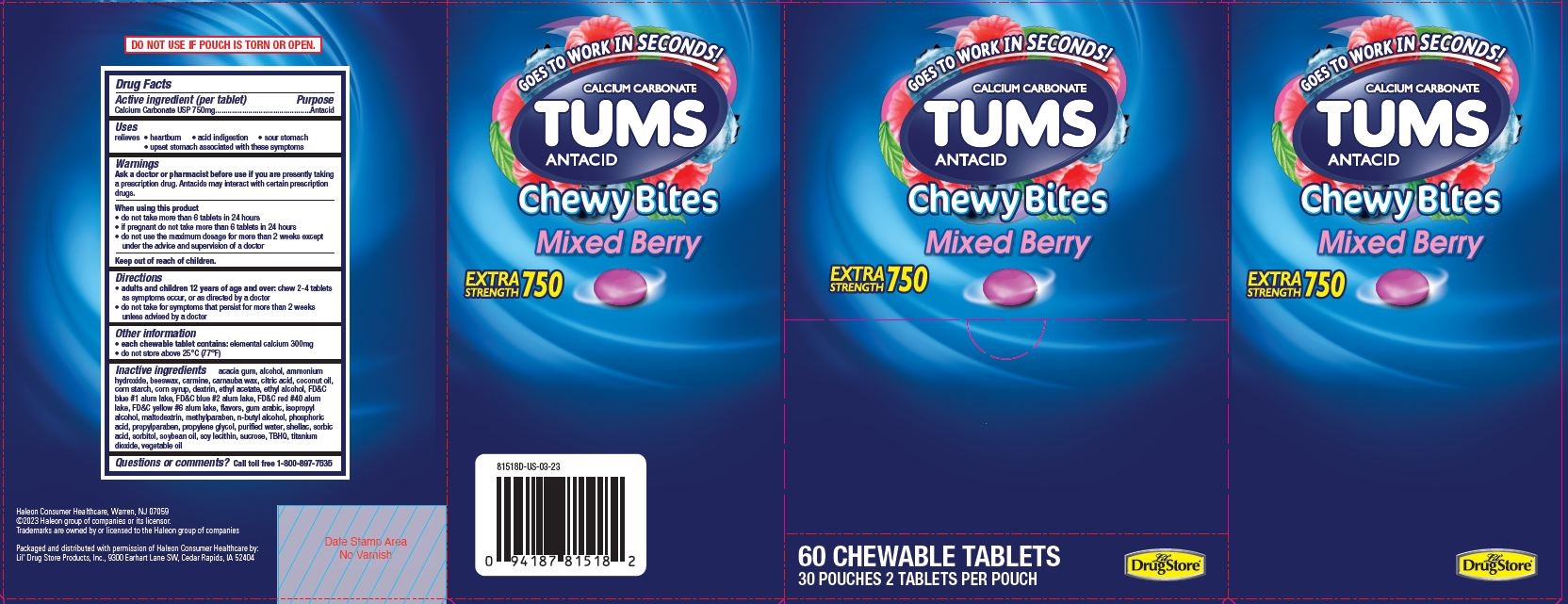 DRUG LABEL: Tums Antacid Chewy Bites
NDC: 66715-8151 | Form: TABLET, CHEWABLE
Manufacturer: Lil' Drug Store products, Inc.
Category: otc | Type: HUMAN OTC DRUG LABEL
Date: 20241120

ACTIVE INGREDIENTS: CALCIUM CARBONATE 750 mg/1 1
INACTIVE INGREDIENTS: WATER; LECITHIN, SOYBEAN; TERT-BUTYLHYDROQUINONE; FD&C BLUE NO. 2; ETHYL ACETATE; ACACIA; CARNAUBA WAX; CORN SYRUP; FD&C BLUE NO. 1; ISOPROPYL ALCOHOL; MALTODEXTRIN; PROPYLENE GLYCOL; CARMINIC ACID; COCONUT OIL; STARCH, CORN; ICODEXTRIN; METHYLPARABEN; PROPYLPARABEN; YELLOW WAX; FD&C RED NO. 40; ALCOHOL; CITRIC ACID MONOHYDRATE; ALUMINUM OXIDE; PHOSPHORIC ACID; SORBIC ACID; SORBITOL; CORN OIL; SOYBEAN OIL; SUCROSE; TITANIUM DIOXIDE; AMMONIA; FD&C YELLOW NO. 6; SHELLAC; BUTYL ALCOHOL

Tums Antacid Chewy Bites, Lil' Drug Store®

Drug Facts

Active ingredient

Active ingredient (per tablet)

Calcium Carbonate USP 750mg

Purpose

Antacid

Uses

relieves

- heartburn
- acid indigestion
- sour stomach
- upset stomach associated with these symptoms

Warnings

Ask a doctor or pharmacist before use if you are presently taking a prescription drug. Antacids may interact with certain prescription drugs.

When using this product

- do not take more than 6 tablets in 24 hours
- if pregnant do not take more than 6 tablets in 24 hours
- do not use the maximum dosage for more than 2 weeks except under the advice and supervision of a doctor

Keep out of reach of children

Directions

- adults and children 12 years of age and over: chew 2-4 tablets as symptoms occur, or as directed by a doctor
- do not take for symptoms that persist for more than 2 weeks unless advised by a doctor

Other information

- each chewable tablet contains: elemental calcium 300mg
- do not store above 25°C (77°F)

Inactive ingredients

acacia gum, alcohol, ammonium hydroxide, beeswax, carmine, carnauba wax, citric acid, coconut oil, corn starch, corn syrup, dextrin, ethyl acetate, ethyl alcohol, FD&C blue #1 alum lake, FD&C blue #2 alum lake, FD&C red #40 alum lake, FD&C yellow #6 alum lake, flavors, gum arabic, isopropyl alcohol, maltodextrin, methylparaben, n-butyl alcohol, phosphoric acid, propylparaben, propylene glycol, purified water, shellac, sorbic acid, sorbitol, soybean oil, soy lecithin, sucrose, TBHQ, titanium dioxide, vegetable oil

Questions or comments

Call toll free 1-800-897-7535

Tums Antacid Chewy Bites, 4ct, Lil' Drug Store® - PDP/Package

GOES TO WORK IN SECONDS!

CALCIUM CARBONATE

TUMS

ANTACID

Chewy Bites

Mixed Berry

EXTRA

STRENGTH 750

[tablet image]

4 CHEWABLE TABLETS

2 POUCHES OF 2 TABLETS EACH

[Lil' Drug Store® logo]

Tums Antacid Chewy Bites, 60ct, Lil' Drug Store® - PDP/Package

GOES TO WORK IN SECONDS!

CALCIUM CARBONATE

TUMS

ANTACID

Chewy Bites

Mixed Berry

EXTRA

STRENGTH 750

[tablet image]

60 CHEWABLE TABLETS

30 POUCHES 2 TABLETS PER POUCH

[Lil' Drug Store® logo]